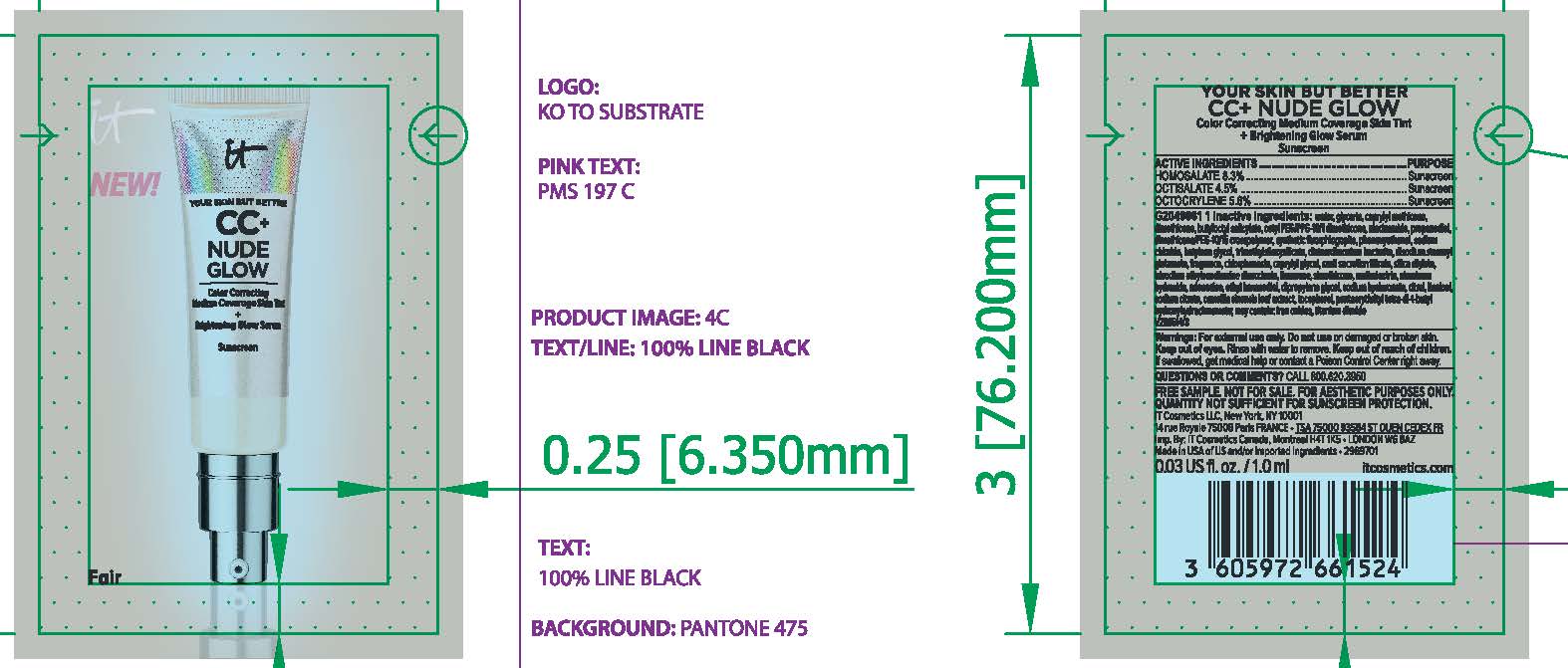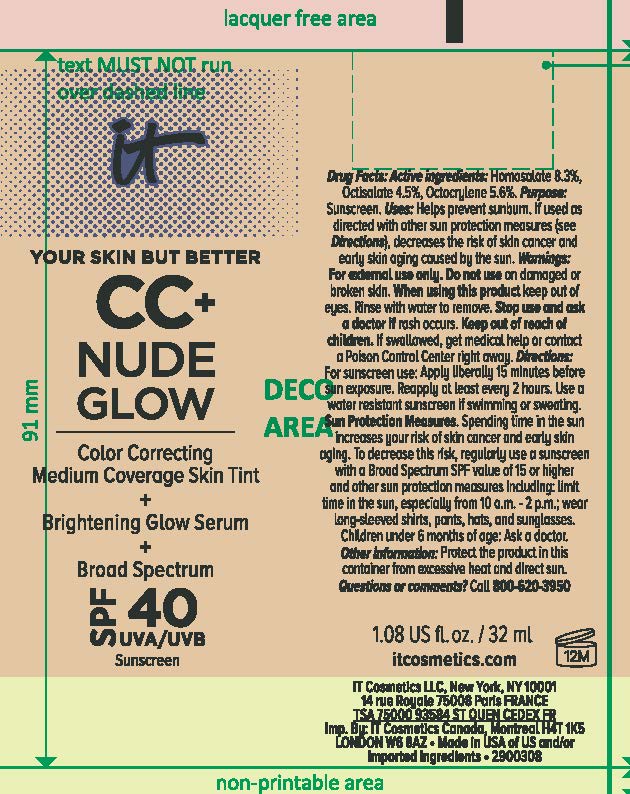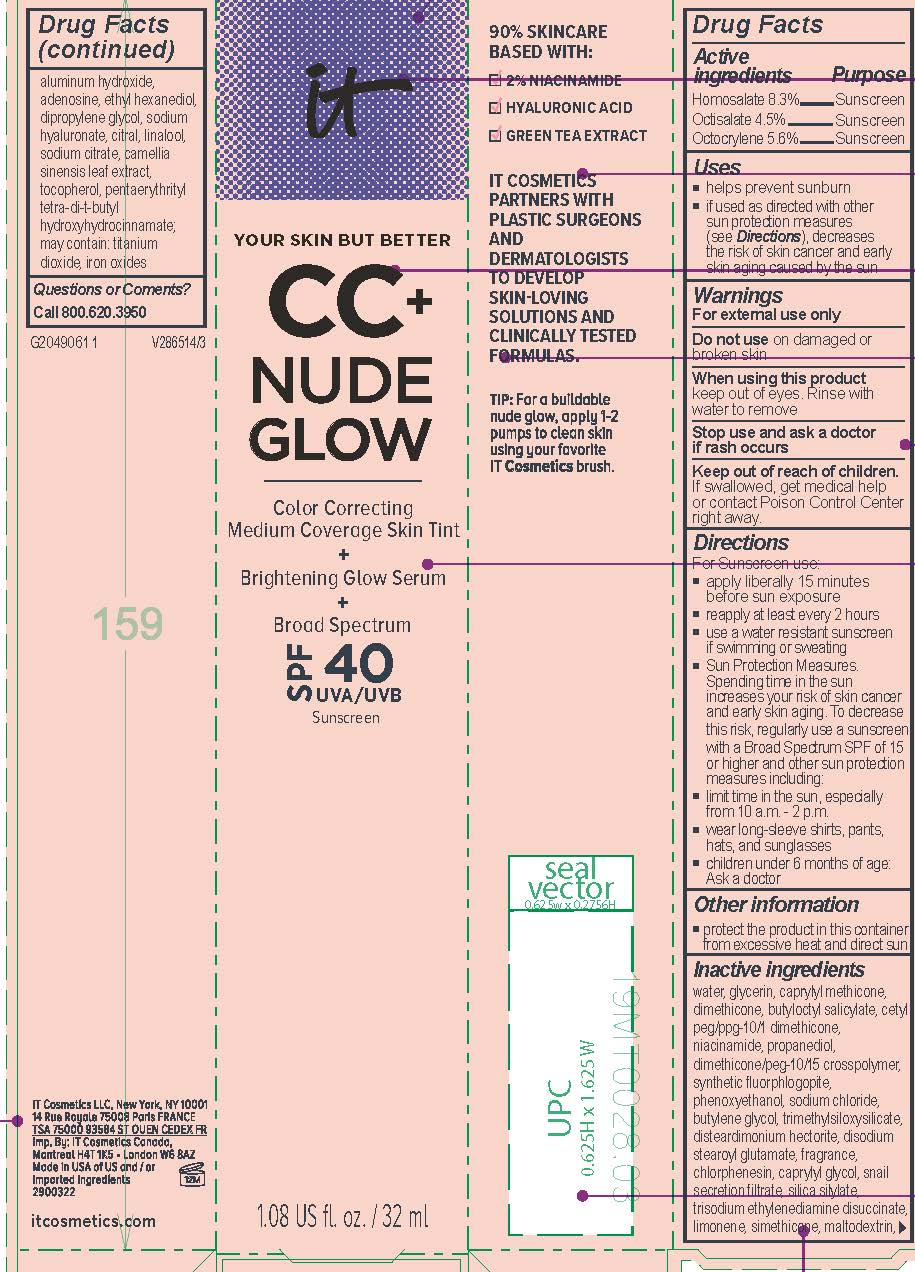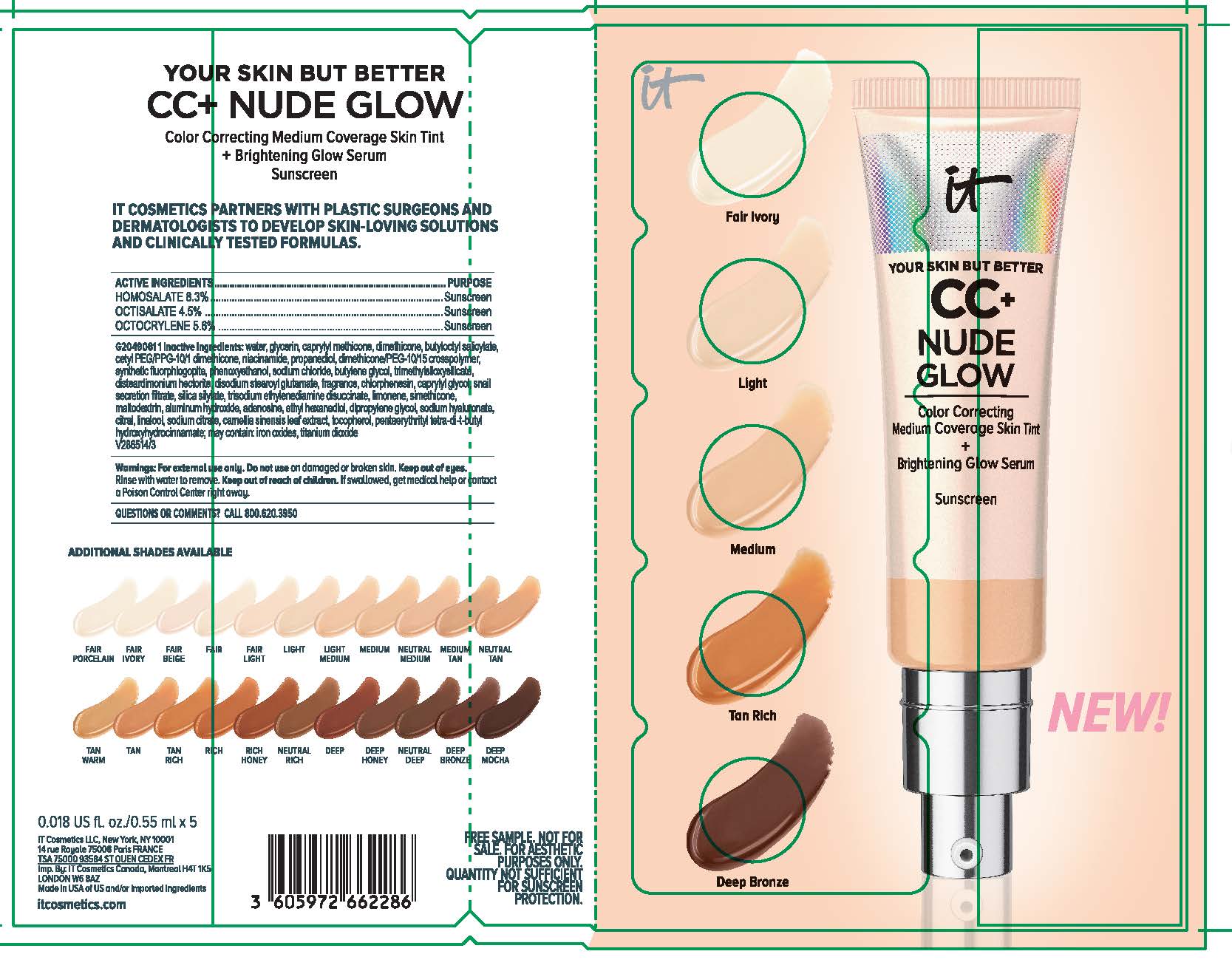 DRUG LABEL: IT Cosmetics Your Skin But Better CC Plus Nude Glow Color Correcting Medium Coverage Skin Tint Brightening Glow Serum Broad Spectrum SPF 40 Sunscreen All Shades
NDC: 69259-5968 | Form: LOTION
Manufacturer: IT COSMETICS, LLC
Category: otc | Type: HUMAN OTC DRUG LABEL
Date: 20231230

ACTIVE INGREDIENTS: HOMOSALATE 83 mg/1 mL; OCTISALATE 45 mg/1 mL; OCTOCRYLENE 56 mg/1 mL
INACTIVE INGREDIENTS: WATER; GLYCERIN; CAPRYLYL TRISILOXANE; DIMETHICONE; BUTYLOCTYL SALICYLATE; NIACINAMIDE; CETYL PEG/PPG-10/1 DIMETHICONE (HLB 2); PROPANEDIOL; DIMETHICONE/PEG-10/15 CROSSPOLYMER; MAGNESIUM POTASSIUM ALUMINOSILICATE FLUORIDE; BUTYLENE GLYCOL; TRIMETHYLSILOXYSILICATE (M/Q 0.6-0.8); PHENOXYETHANOL; SODIUM CHLORIDE; DISTEARDIMONIUM HECTORITE; DISODIUM STEAROYL GLUTAMATE; CHLORPHENESIN; TRISODIUM ETHYLENEDIAMINE DISUCCINATE; LIMONENE, (+)-; MALTODEXTRIN; ALUMINUM HYDROXIDE; ADENOSINE; DIPROPYLENE GLYCOL; ETHOHEXADIOL; HYALURONATE SODIUM; CITRAL; SODIUM CITRATE; LINALOOL, (+/-)-; GREEN TEA LEAF; TOCOPHEROL; PENTAERYTHRITOL TETRAKIS(3-(3,5-DI-TERT-BUTYL-4-HYDROXYPHENYL)PROPIONATE); TITANIUM DIOXIDE; FERRIC OXIDE RED

Drug Facts

Active ingredients

Homosalate 8.3%

Octisalate 4.5%

Octocrylene 5.6%

Purpose

Sunscreen

Uses

- helps prevent sunburn
- if used as directed with other sun protection measures (see Directions), decreases the risk of skin cancer and early skin aging caused by the sun

Warnings

For external use only

Do not use

on damaged or broken skin

When using this product

keep out of eyes. Rinse with water to remove.

Stop use and ask a doctor if

rash occurs

Keep out of reach of children.

If swallowed, get medical help or contact a Poison Control Center right away.

Directions

For sunscreen use:

● apply liberally 15 minutes before sun exposure

● reapply at least every 2 hours

● use a water resistant sunscreen if swimming or sweating

● Sun Protection Measures. Spending time in the sun increases your risk of skin cancer and early skin aging. To decrease this risk,

regularly use a sunscreen with a Broad Spectrum SPF value of 15 or higher and other sun protection measures including:

● limit time in the sun, especially from 10 a.m. – 2 p.m.

● wear long-sleeved shirts, pants, hats, and sunglasses

● children under 6 months of age: Ask a doctor

Other information

protect the product in this container from excessive heat and direct sun

Inactive ingredients

water, glycerin, caprylyl methicone, dimethicone, butyloctyl salicylate, niacinamide, cetyl PEG/PPG-10/1 dimethicone, propanediol, dimethicone/PEG-10/15 crosspolymer, synthetic fluorphlogopite, butylene glycol, trimethylsiloxysilicate, phenoxyethanol, sodium chloride, disteardimonium hectorite, disodium stearoyl glutamate, fragrance, chlorphenesin, snail secretion filtrate, silica silylate, trisodium ethylenediamine disuccinate, limonene, maltodextrin, aluminum hydroxide, adenosine, dipropylene glycol, ethyl hexanediol, sodium hyaluronate, citral, sodium citrate, linalool, camellia sinensis leaf extract, tocopherol, pentaerythrityl tetra-di-t-butyl hydroxyhydrocinnamate; may contain: titanium dioxide, iron oxides

Questions or comments?

Call 800-620-3956